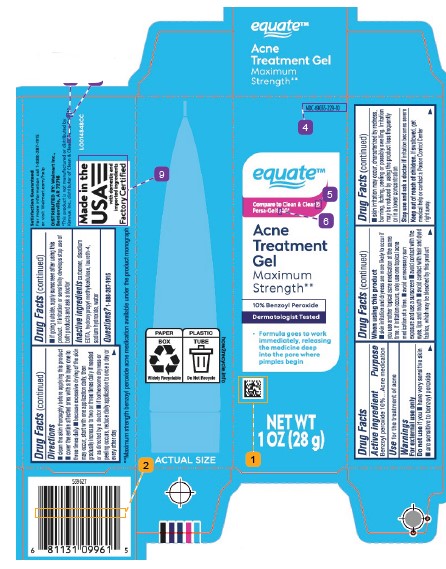 DRUG LABEL: Acne Treatment
NDC: 49035-229 | Form: GEL
Manufacturer: Walmart Inc.
Category: otc | Type: HUMAN OTC DRUG LABEL
Date: 20260227

ACTIVE INGREDIENTS: BENZOYL PEROXIDE 100 mg/1 g
INACTIVE INGREDIENTS: LAURETH-4; SODIUM HYDROXIDE; WATER; CARBOXYPOLYMETHYLENE; EDETATE DISODIUM; HYPROMELLOSE, UNSPECIFIED

Equate 229.001/229AC-AD
10% Benzoyl Peroxide Acne Medicated Gel

Active ingredient

Benzoyl peroxide 10%

Purpose

Acne medication

Use

for the treatment of acne

Warnings

For external use only

Do not use if you

- have very sensitive skin
- are sensitive to benzoyl peroxide

When using this product

- skin irritation and dryness is more likely to occur if you use another topical acne medication at the same time. If irritation occurs, only use one topical acne medication at a time
- avoid unnecessary sun exposure and use a sunscreen
- avoid contact with eyes, lips and mouth
- avoid contact with hair and dyed fabrics, which may be bleached by this product
- skin irritation may occur, characterized by redness, buring, itching, peeling or possible swelling. Irritation may be reduced by using the product less frequently or in a lower concentration

Stop use and ask a doctor if

irritation becomes severe

Keep out of reach of children.

If swallowed, get medical help or contact a Poison Control Center right away.

Directions

- clean the skin thoroughly before applying this product
- cover the entire affected area with a thin layer one to three times daily
- because excessive drying of the skin may occur, start with one application daily, then gradually increase to two or three times daily if needed or as directed by a doctor
- if bothersome dryness or peeling occurs, reduce daily application to once a day or every other day
- if going outside, apply sunscreen after using this product. If irritation or sensitivity develops stop use of both products and ask a doctor

Inactive ingredients

carbomer, disodium EDTA, hydroxypropyl methylcellulose, laureth-4, sodium hydroxide, water

Questions?

1-888-287-1915

Claims

**Maximum strength benzoyl peroxide acne medication available under the product monograph.

Satisfaction guaranteed - For more information call 1-888-287-1915 or visit Walmart.com/help

ADVERSE REACTION

Distributed by: Walmart Inc.,

Bentonville, AR 72716

PAPER BOX

Widely Recyclable

PLASTIC TUBE

Do Not Recycle

how2recycle.info

Made in the USA with domestic and imported ingredients

Factory Certified

Disclaimer

*This product is not manufactured or distributed by Kenvue, Inc., distributor of Clean & Clear® Persa-Gel 10.

Top Panel Claims

equate

Acne Treatment Gel

Maximum Strength**

principal display panel

NDC 49035-229-10

equate™

Compare to Clean & Clear® Persa-Gel 10*

ACNE TREATMENT GEL

Benzoyl Peroxide 10%

Maximum Strength**

10% Benzoyl Peroxide

Dermatologist Tested

- Formula goes to work immediately, releasing the medicine deep into the pore where pimples begin

NET WT 1 OZ (28 g)